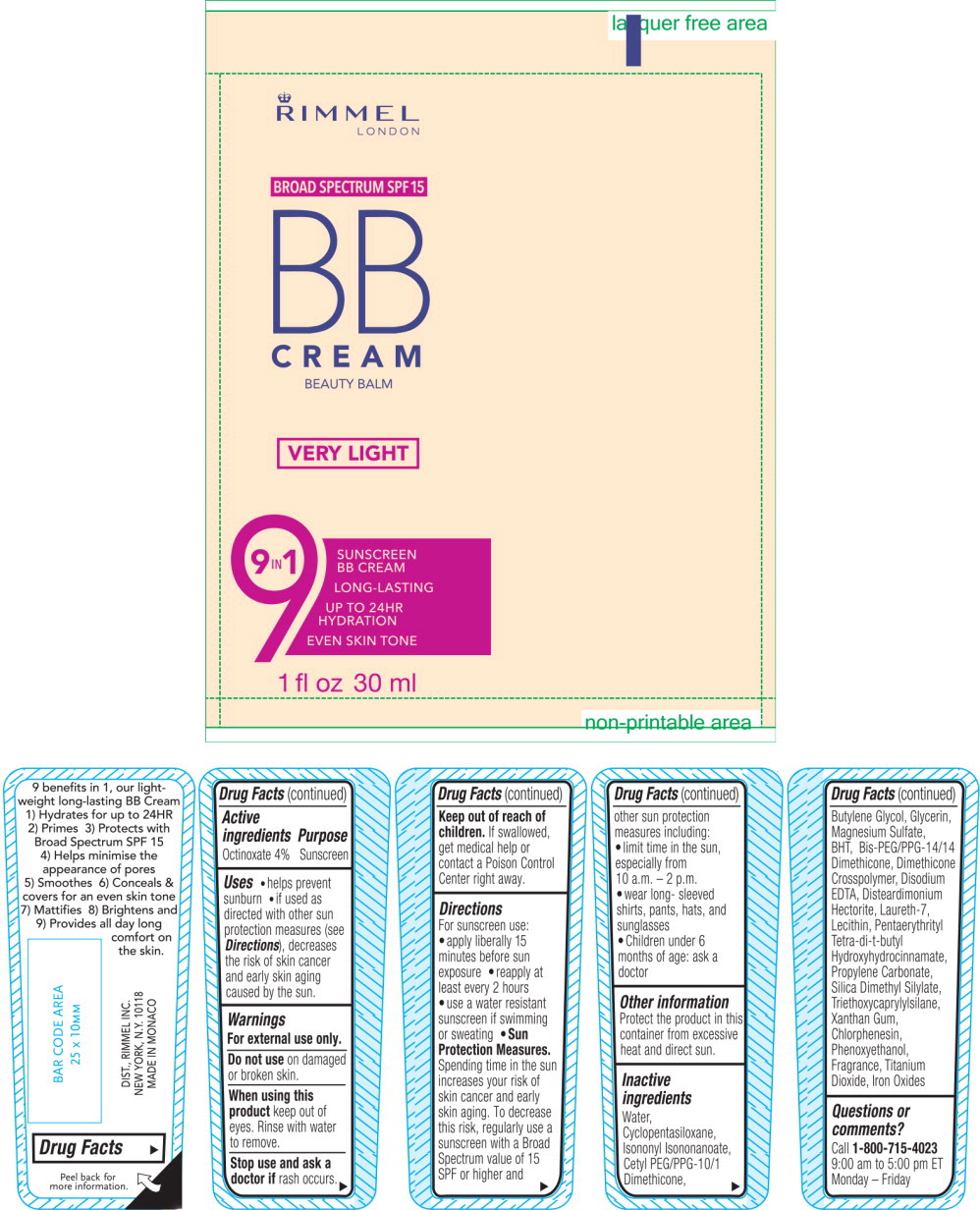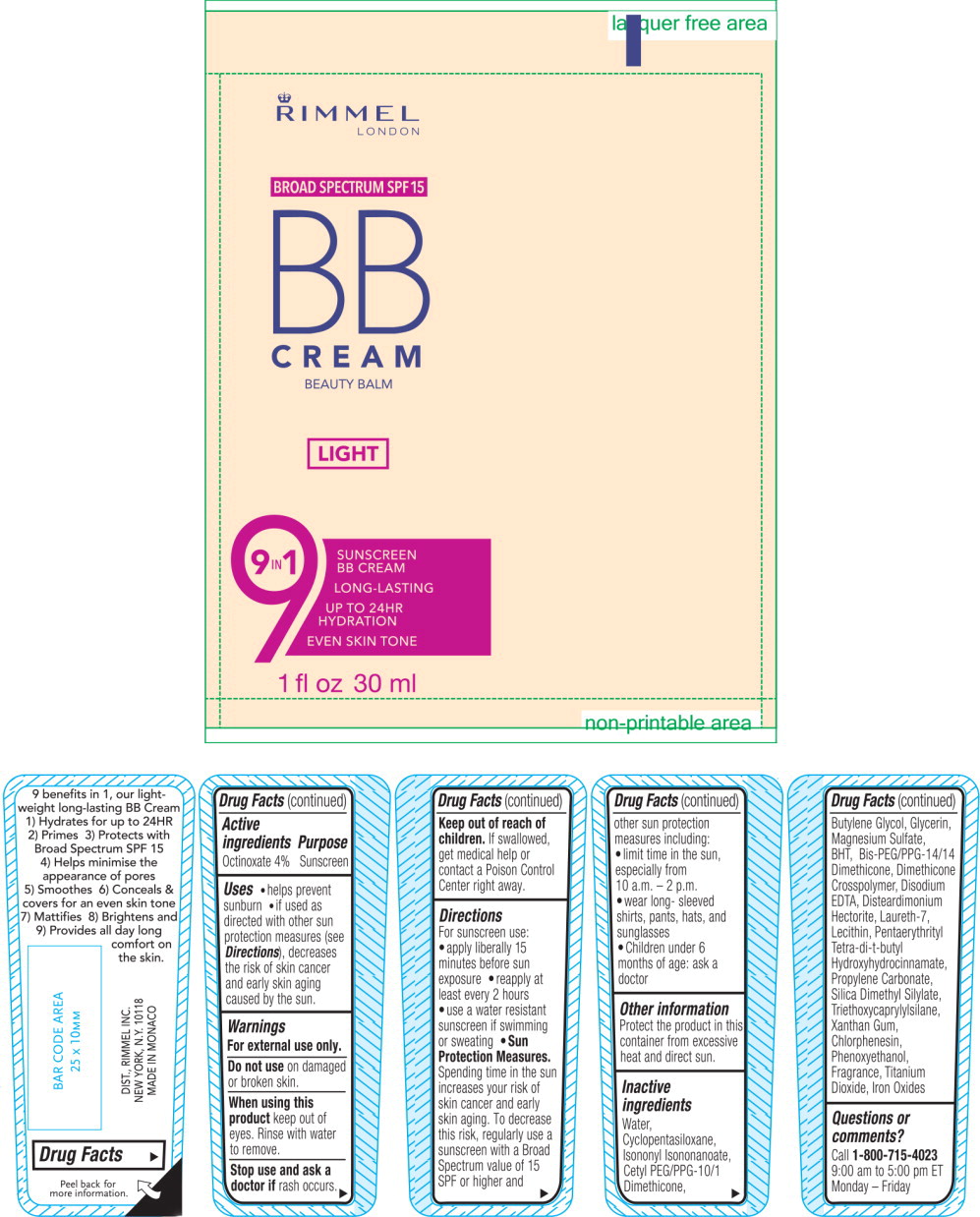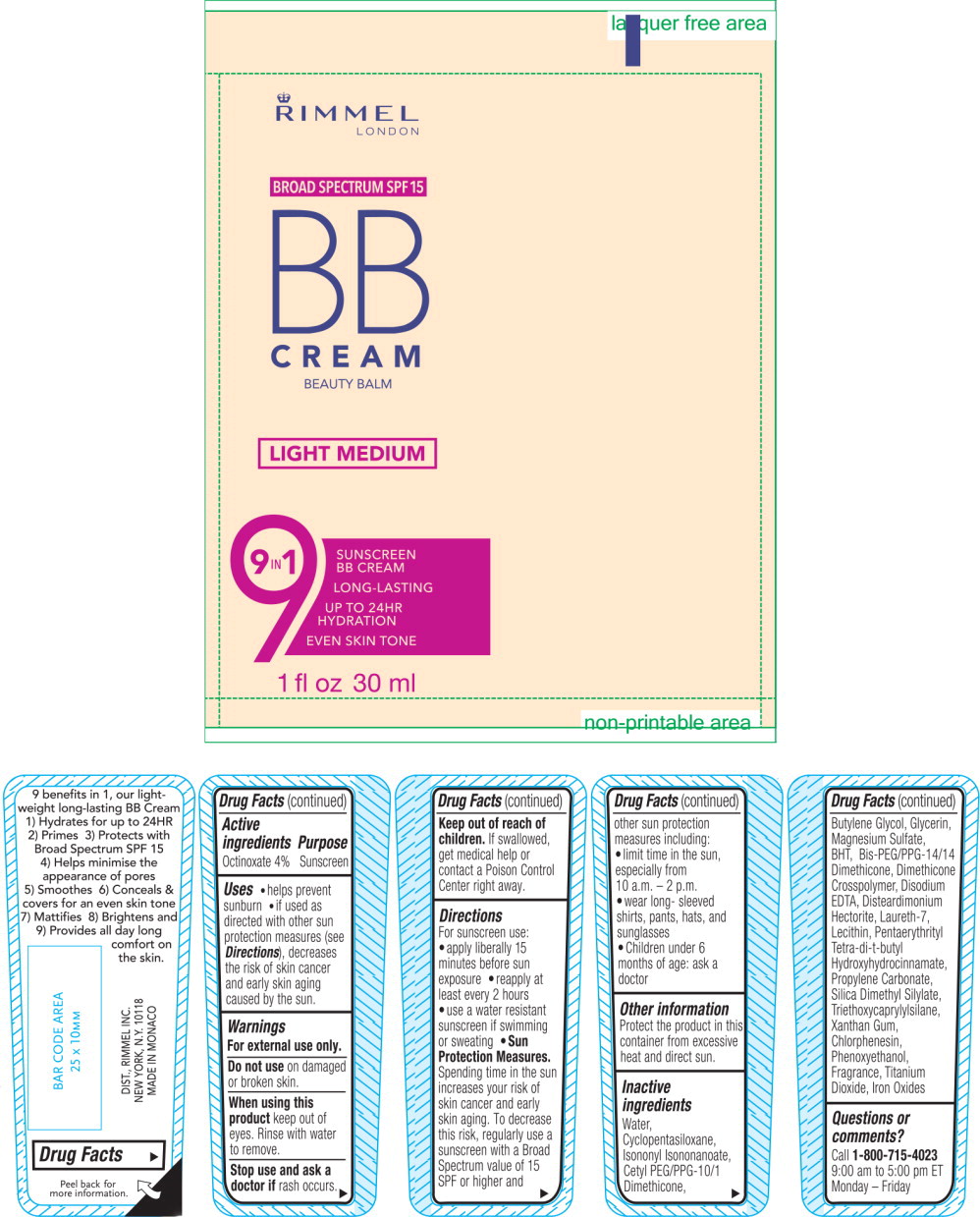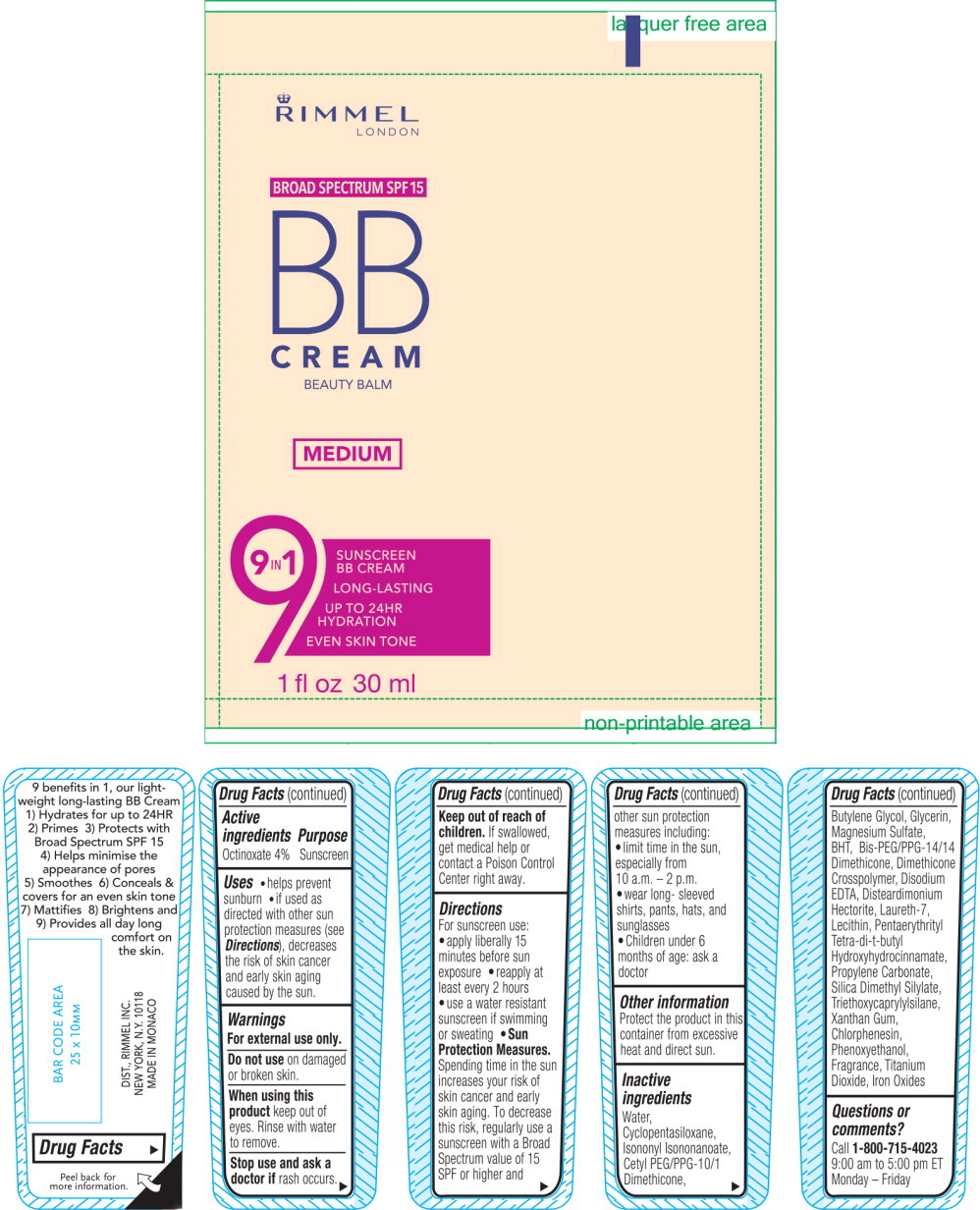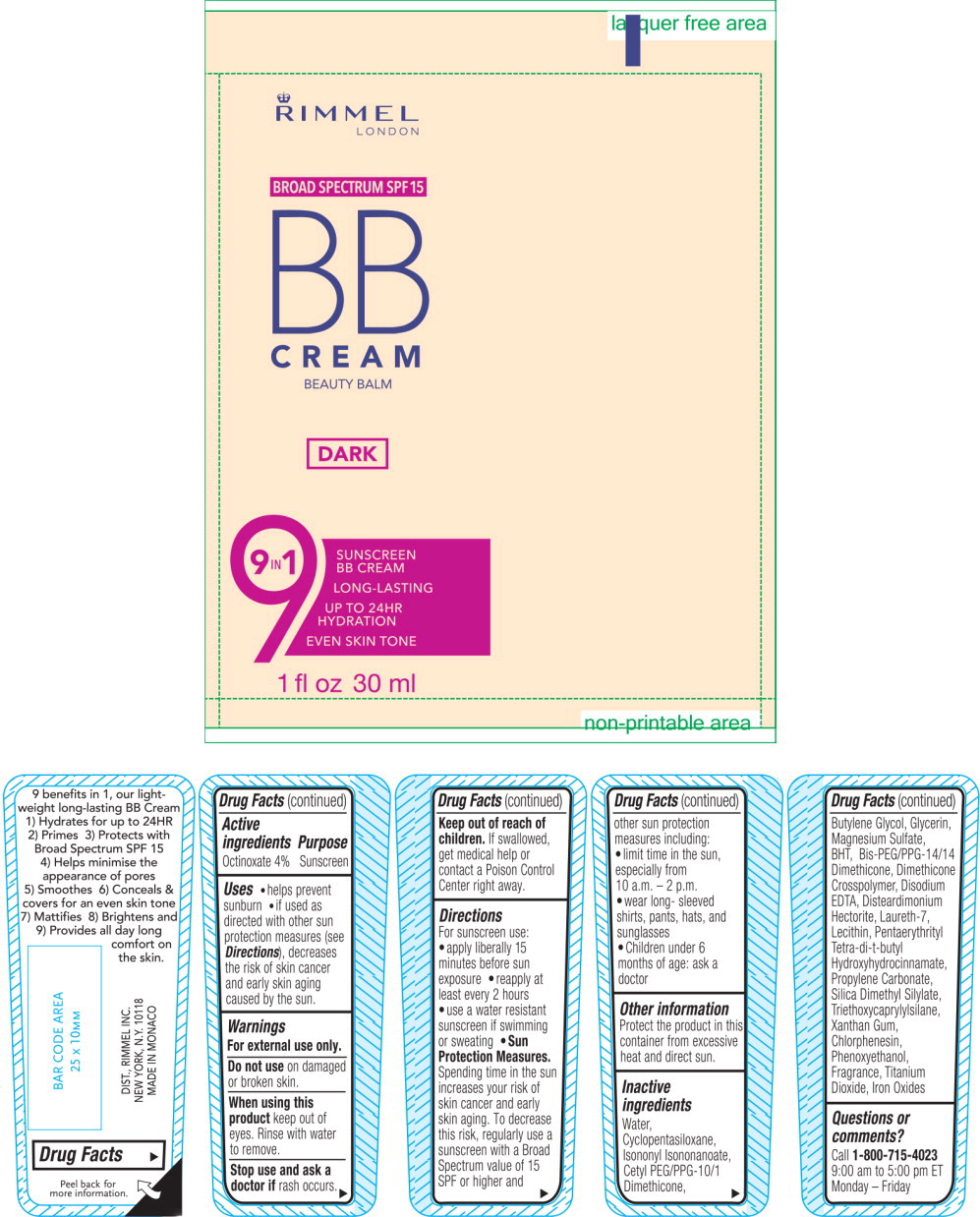 DRUG LABEL: Rimmel BB Cream Beauty Balm 

NDC: 76485-1074 | Form: CREAM
Manufacturer: Rimmel Inc.
Category: otc | Type: HUMAN OTC DRUG LABEL
Date: 20201026

ACTIVE INGREDIENTS: OCTINOXATE 1.3 g/30 mL
INACTIVE INGREDIENTS: WATER; CYCLOMETHICONE 5; ISONONYL ISONONANOATE; BUTYLENE GLYCOL; GLYCERIN; MAGNESIUM SULFATE, UNSPECIFIED FORM; BUTYLATED HYDROXYTOLUENE; BIS-PEG/PPG-14/14 DIMETHICONE; DIMETHICONE CROSSPOLYMER (450000 MPA.S AT 12% IN CYCLOPENTASILOXANE); EDETATE DISODIUM ANHYDROUS; DISTEARDIMONIUM HECTORITE; LAURETH-7; PENTAERYTHRITOL TETRAKIS(3-(3,5-DI-TERT-BUTYL-4-HYDROXYPHENYL)PROPIONATE); PROPYLENE CARBONATE; SILICA DIMETHYL SILYLATE; TRIETHOXYCAPRYLYLSILANE; XANTHAN GUM; CHLORPHENESIN; PHENOXYETHANOL; TITANIUM DIOXIDE; FERRIC OXIDE RED

Rimmel BB Cream Beauty Balm

Active ingredients

Octinoxate 4%

Purpose

Sunscreen

Uses

- helps prevent sunburn
- if used as directed with other sun protection measures (see Directions), decreases the risk of skin cancer and early skin aging caused by the sun.

Warnings

For external use only.

Do not use on damaged or broken skin.

When using this product keep out of eyes, Rinse with water to remove.

Stop use and ask a doctor if rash occurs.

Keep out of reach of children. If swallowed, get medical help or contact a Poison Control Center right away.

Directions

For sunscreen use:

- apply liberally 15 minutes before sun exposure
- reapply at least every 2 hours
- use a water resistant sunscreen if swimming or sweating
- Sun Protection Measures. Spending time in the sun increases your risk of skin cancer and early skin aging. To decrease this risk, regularly use a sunscreen with a Broad Spectrum value of 15 SPF or high and other sun protection measures including:
- limit time in the sun, especially from 10 a.m. - 2 p.m.
- wear long - sleeved shirts, pants, hats, and sunglasses
- Children under 6 months of age: ask a doctor

Other information

Protect the product in this container from excessive heat and direct sun.

Inactive ingredients

Water, Cyclopentasiloxane, Isononyl Isononanoate, Cetyl PEG/PPG-10/1 Dimethicone, Butylene Glycol, Glycerin, Magnesium Sulfate, BHT, Bis-PEG/PPG-14/14 Dimethicone, Dimethicone Crosspolymer, Disodium EDTA, Disteardimonium Hectorite, Laureth-7, Lecithin, Pentaerythrityl Tetra-di-t-butyl Hydroxyhydrocinnamate, Propylene Carbonate, Silica Dimethyl Silylate, Triethoxycaprylylsilane, Xanthan Gum, Chlorphenesin, Phenoxyethanol, Fragrance, Titanium Dioxide, Iron Oxides

Questions or comments?

Call 1-800-715-4023

9:00 am to 5:00 pm ET

Monday - Friday

Principal Display Panel - 30 mL Bottle Very Light Label

RIMMEL

LONDON

BROAD SPECTRUM SPF15

BB CREAM

BEAUTY BALM

VERY LIGHT

9 in1

SUNSCREEN BB CREAM

LONG-LASTING

UP TO 24HR HYDRATION

EVEN SKIN TONE

1 fl oz 30 ml

Principal Display Panel - 30 mL Bottle Light Label

RIMMEL

LONDON

BROAD SPECTRUM SPF15

BB CREAM

BEAUTY BALM

LIGHT

9 in1

SUNSCREEN BB CREAM

LONG-LASTING

UP TO 24HR HYDRATION

EVEN SKIN TONE

1 fl oz 30 ml

Principal Display Panel - 30 mL Bottle Light Medium Label

RIMMEL

LONDON

BROAD SPECTRUM SPF15

BB CREAM

BEAUTY BALM

LIGHT MEDIUM

9 in1

SUNSCREEN BB CREAM

LONG-LASTING

UP TO 24HR HYDRATION

EVEN SKIN TONE

1 fl oz 30 ml

Principal Display Panel - 30 mL Bottle Medium Label

RIMMEL

LONDON

BROAD SPECTRUM SPF15

BB CREAM

BEAUTY BALM

MEDIUM

9 in1

SUNSCREEN BB CREAM

LONG-LASTING

UP TO 24HR HYDRATION

EVEN SKIN TONE

1 fl oz 30 ml

Principal Display Panel - 30 mL Bottle Dark Label

RIMMEL

LONDON

BROAD SPECTRUM SPF15

BB CREAM

BEAUTY BALM

Dark

9 in1

SUNSCREEN BB CREAM

LONG-LASTING

UP TO 24HR HYDRATION

EVEN SKIN TONE

1 fl oz 30 ml